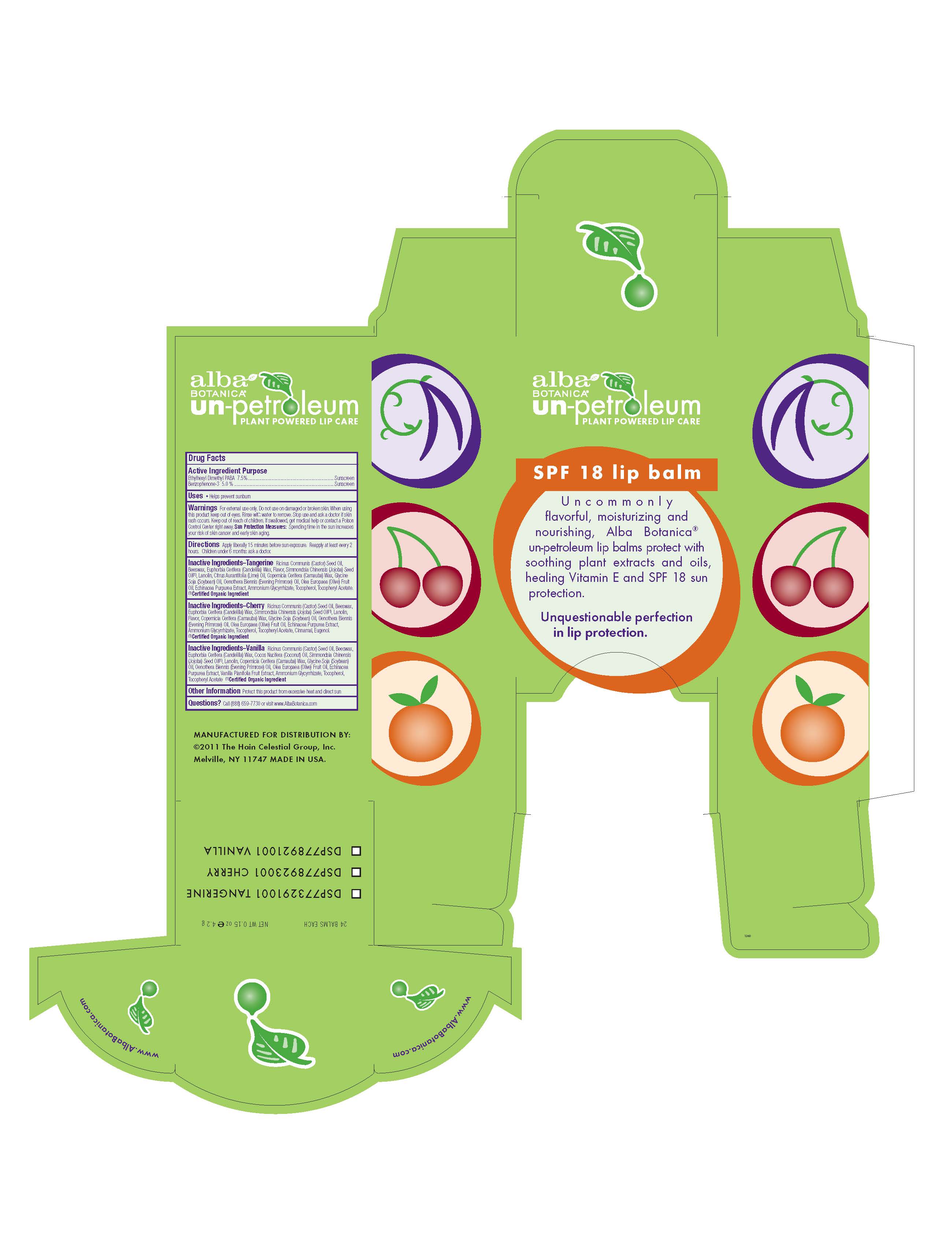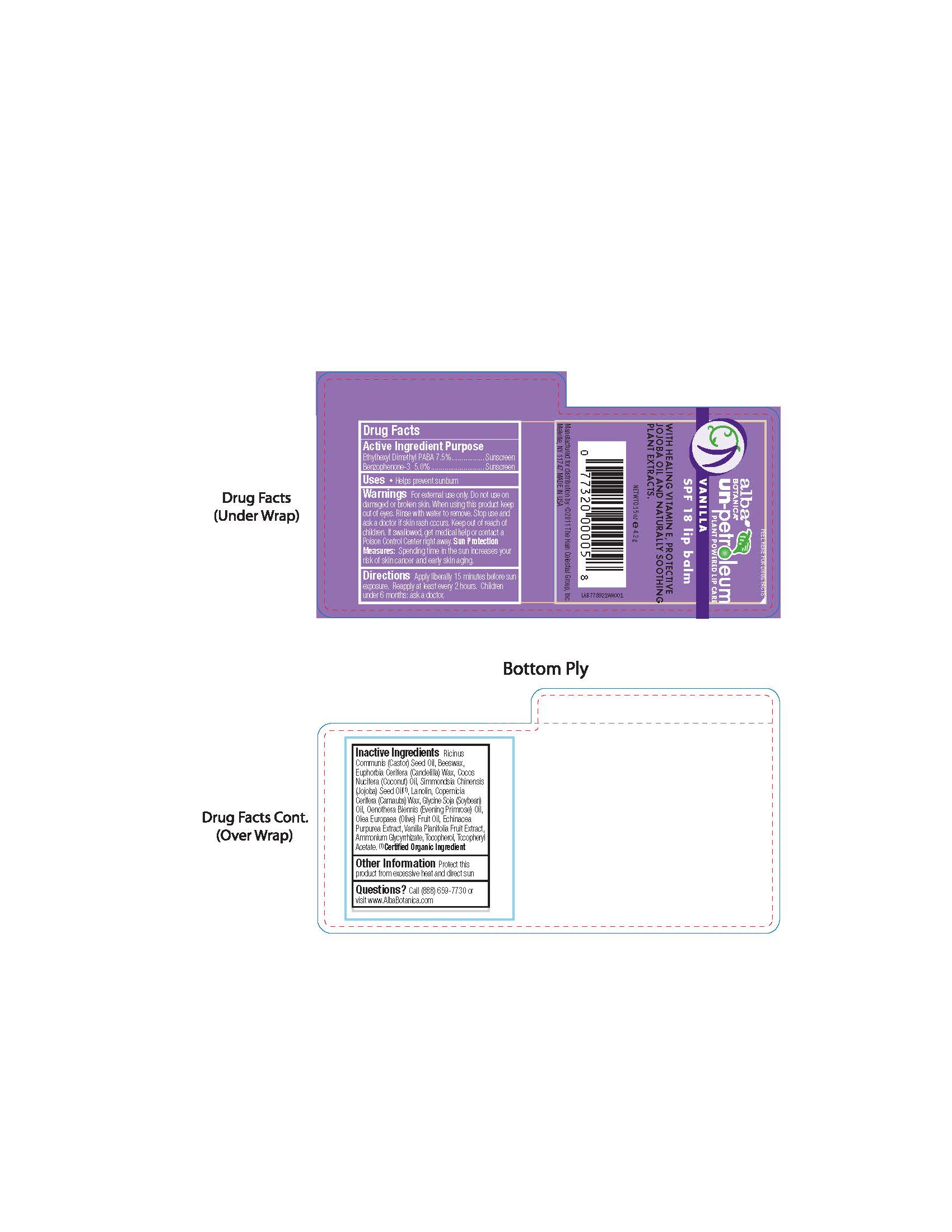 DRUG LABEL: Alba Botanica UN-petroleum Vanilla SPF18 Lip Balm
NDC: 61995-2921 | Form: STICK
Manufacturer: The Hain Celestial Group, Inc.
Category: otc | Type: HUMAN OTC DRUG LABEL
Date: 20120510

ACTIVE INGREDIENTS: PADIMATE O 7.5 g/100 g; OXYBENZONE 5.0 g/100 g
INACTIVE INGREDIENTS: CASTOR OIL ; YELLOW WAX; CANDELILLA WAX; JOJOBA OIL; LANOLIN ; CARNAUBA WAX; SOYBEAN OIL; EVENING PRIMROSE OIL ; OLIVE OIL; ECHINACEA PURPUREA; AMMONIUM GLYCYRRHIZATE; TOCOPHEROL ; .ALPHA.-TOCOPHEROL ACETATE ; COCONUT OIL; VANILLA

Drug Facts

ACTIVE INGREDIENT

Ethylhexyl Dimethyl PABA 7.5%

Benzophenone-3 5.0%

PURPOSE

Sunscreen

INDICATIONS AND USAGE

Helps prevent sunburn

WARNINGS

For external use only. Do not use on damaged or broken skin. When using this product keep out of eyes. Rinse with water to remove.Stop use and ask a doctor if skin rash occurs.

Keep out of reach of children. If swallowed, get medical help or contact Poison Center right away.

DOSAGE AND ADMINISTRATION

Apply liberally 15 minutes before sun exposure. Reapply at least every 2 hours. Children under 6 mos ask a doctor.

Skin Protection Measures:Spending time in the sun increases your risk of skin cancer and early skin aging.

INACTIVE INGREDIENT

Ricinus Communis (Castor) Seed Oil, Beeswax, Euphorbia Cerifera (Candelilla) Wax, Cocos Nucifera (Coconut) Oil, Simmondsia Chinensis (Jojoba) Seed Oil (1), Lanolin, Copernicia Cerifera (Carnauba) Wax, Glycine Soja (Soybean) Oil, Oenothera Biennis (Evening Primrose) Oil, Olea Europaea (0live)Fruit Oil, Echinacea Purpurea Extract, Vanilla Planifolia Fruit Extract, Ammonium Glycyrrhizate, Tocopherol, Tocopheryl Acetate.

(1) Certified Organic Ingredient

QUESTIONS

Questions? Call 888-659-7730 or visit www.AlbaBotanica.com